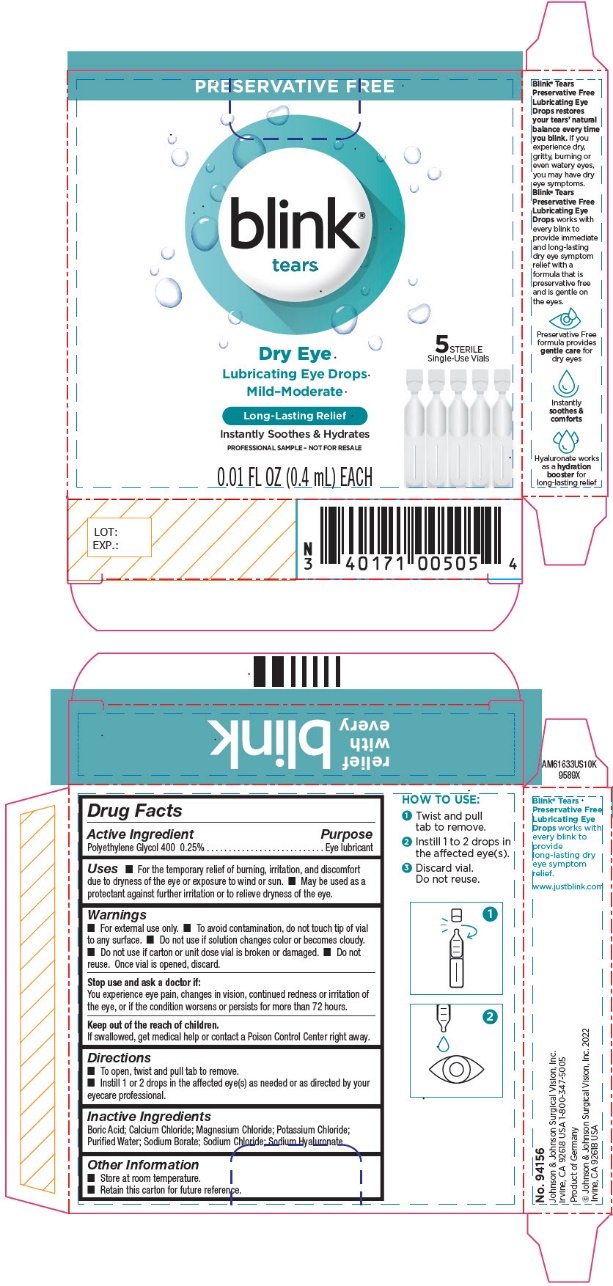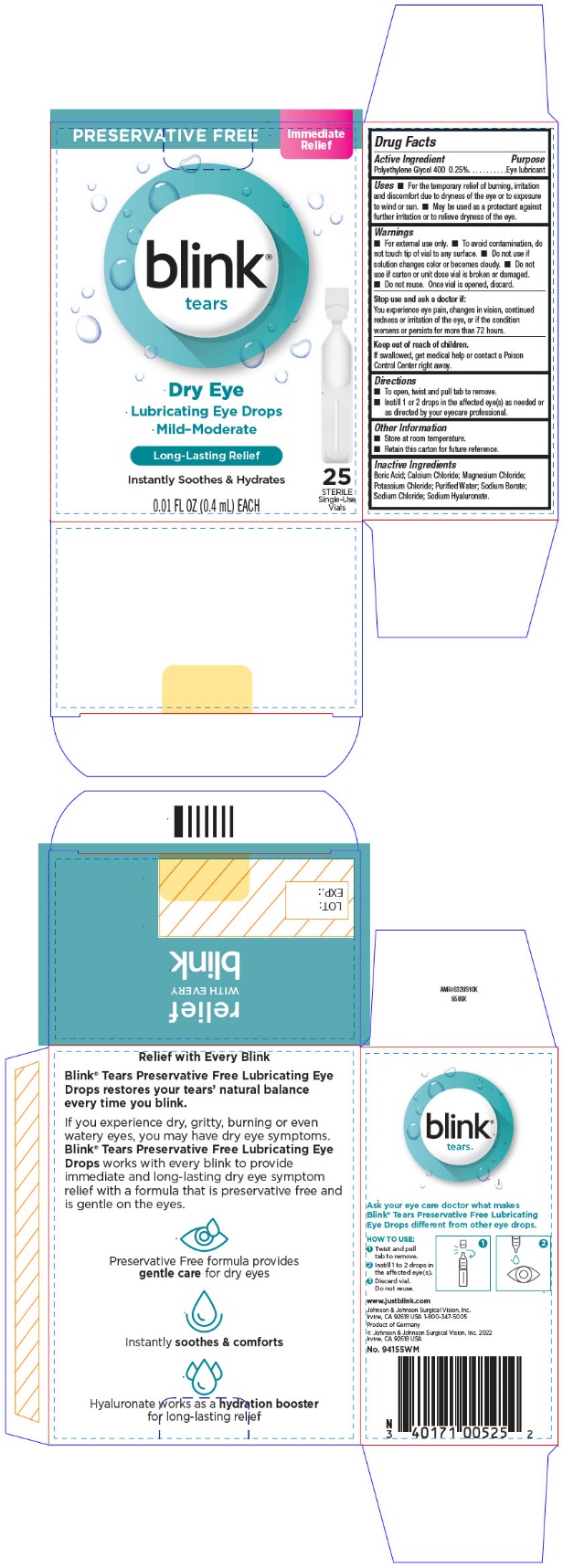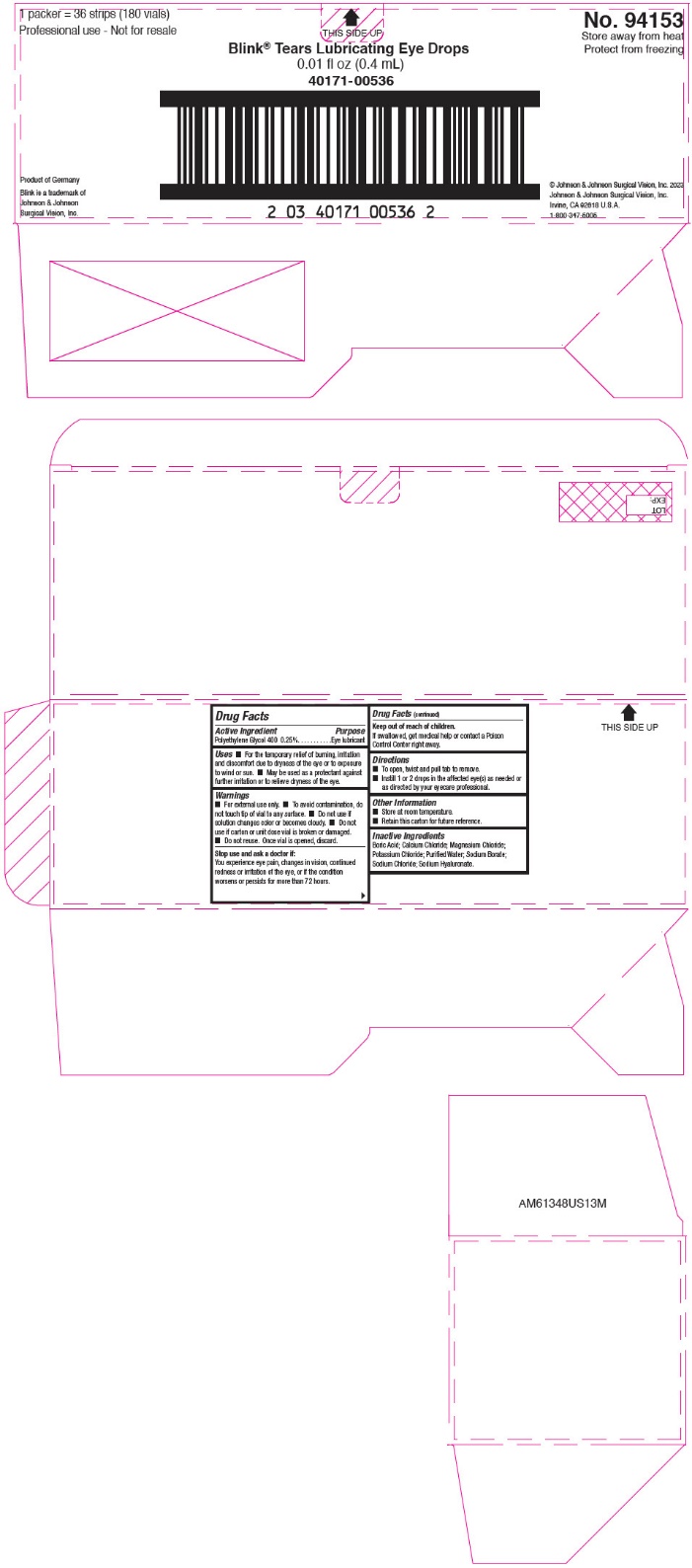 DRUG LABEL: blink tears
NDC: 40171-005 | Form: SOLUTION/ DROPS
Manufacturer: Bausch & Lomb Incorporated
Category: otc | Type: HUMAN OTC DRUG LABEL
Date: 20240920

ACTIVE INGREDIENTS: POLYETHYLENE GLYCOL 400 2.5 mg/1 mL
INACTIVE INGREDIENTS: BORIC ACID; CALCIUM CHLORIDE; MAGNESIUM CHLORIDE; POTASSIUM CHLORIDE; WATER; SODIUM BORATE; SODIUM CHLORIDE; HYALURONATE SODIUM

Drug Facts

OTC - ACTIVE INGREDIENT SECTION

Polyethylene Glycol 400 0.25%

Purpose

Eye lubricant

Uses

- For the temporary relief of burning, irritation and discomfort due to dryness of the eye or exposure to wind or sun.
- May be used as a protectant against further irritation or to relieve dryness of the eye.

WARNINGS

- For external use only.
- To avoid contamination, do not touch tip of vial to any surface.
- Do not use if solution changes color or becomes cloudy.
- Do not use if carton of unit dose vial is broken or damaged.
- Do not reuse. Once vial is opened, discard.

Stop use and ask doctor if:

You experience eye pain, changes in vision, continued redness or irritation of the eye, or if the condition worsens or persists for more than 72 hours.

OTC - KEEP OUT OF REACH OF CHILDREN SECTION

If swallowed, get medical help or contact a Poison Control Center right away.

Directions

- To open, twist and pull tab to remove.
- Instill 1 or 2 drops in the affected eye(s) as needed or as directed by your eyecare professional.

Other Information

- Store at room temperature.
- Retain this carton for future reference.

INACTIVE INGREDIENT SECTION

Boric Acid, Calcium Chloride, Magnesium Chloride, Potassium Chloride, Purified Water, Sodium Borate, Sodium Chloride, Sodium Hyaluronate.

OTC - QUESTIONS SECTION

In the U.S. call 1-800-347-5005

www.yourhealthyeyes.com

PRINCIPAL DISPLAY PANEL - 5 Vial Carton

PRESERVATIVE FREE

blink®
tears

Dry Eye
Lubricating Eye Drops
Mild-Moderate

5 STERILE
Single-Use Vials

Long-Lasting Relief

Instantly Soothes & Hydrates
PROFESSIONAL SAMPLE - NOT FOR RESALE

0.01 FL OZ (0.4 mL) EACH

PRINCIPAL DISPLAY PANEL - 25 Vial Carton

PRESERVATIVE FREE

Immediate
Relief

blink®
tears

Dry Eye
Lubricating Eye Drops
Mild-Moderate

Long-Lasting Relief

Instantly Soothes & Hydrates

0.01 FL OZ (0.4 mL) EACH

25
STERILE
Single-Use
Vials

PRINCIPAL DISPLAY PANEL - 180 Vial Carton

1 packer = 36 strips (180 vials)

Professional use - Not for resale

THIS SIDE UP

No. 94153
Store away from heat
Protect from freezing

Blink®Tears Lubricating Eye Drops
0.01 fl oz (0.4 mL)
40171-00536

Product of Germany

Blink is a trademark of
Johnson & Johnson
Surgical Vision, Inc.

© Johnson & Johnson Surgical Vision, Inc. 2023
Johnson & Johnson Surgical Vision, Inc.
Irvine, CA 92618 U.S.A.
1-800-347-5005